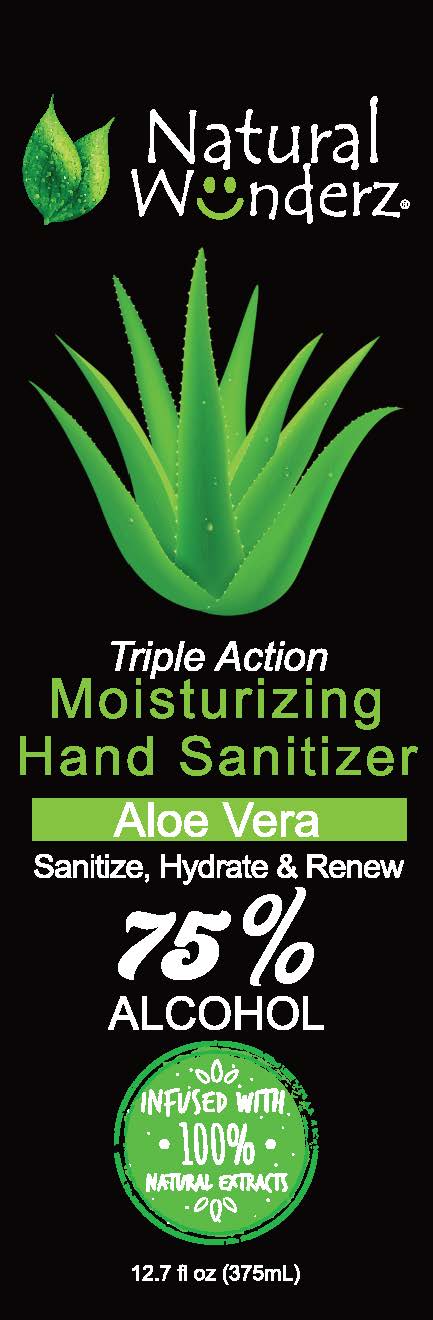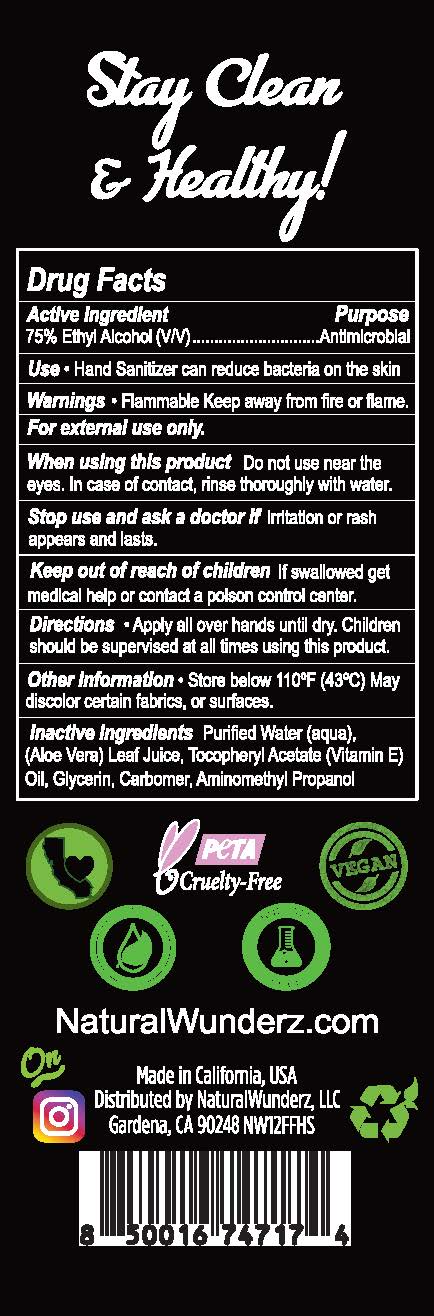 DRUG LABEL: Natural Wunderz Moisturizing Hand Sanitizer
NDC: 79360-101 | Form: GEL
Manufacturer: Natural Wunderz, LLC
Category: otc | Type: HUMAN OTC DRUG LABEL
Date: 20200625

ACTIVE INGREDIENTS: ALCOHOL 75 mL/100 mL
INACTIVE INGREDIENTS: WATER; ALOE VERA LEAF; .ALPHA.-TOCOPHEROL ACETATE; GLYCERIN; CARBOMER HOMOPOLYMER, UNSPECIFIED TYPE; AMINOMETHYLPROPANOL; CHROMIUM HYDROXIDE GREEN

Natural Wunderz - Moisturizing Hand Sanitizer - 75% Alcohol

ACTIVE INGREDIENT

Ethyl Alcohol 75% v/v

PURPOSE

ANTIMICROBIAL

USE

Hand sanitizer can reduce bacteria on the skin

WARNINGS

Flammable Keep away from fire or flame.

For external use only.

When using this product Do not use near the eyes. In case of contact, rinse thoroughly with water.

Stop use and ask a doctor if irritation or rash appears and lasts.

Keep out of reach of children.

If swallowed, get medical help or contact a Poison Control Center right away.

DIRECTIONS

Apply all over hands until dry. Children should be supervised at all times using this product.

INACTIVE INGREDIENTS

Purified Water (Aqua), Aloe Barbadensis (Aloe Vera) Leaf Juice, Tocopheryl Acetate (Vitamin E) Oil, Glycerin, Carbomer, Aminomethyl Propanol, Fragrance (Parfum), Hydrated Chromium Oxide BC CI 77288

OTHER INFORMATION

Store below 110°F (43°C). May discolor certain fabrics, or surfaces.